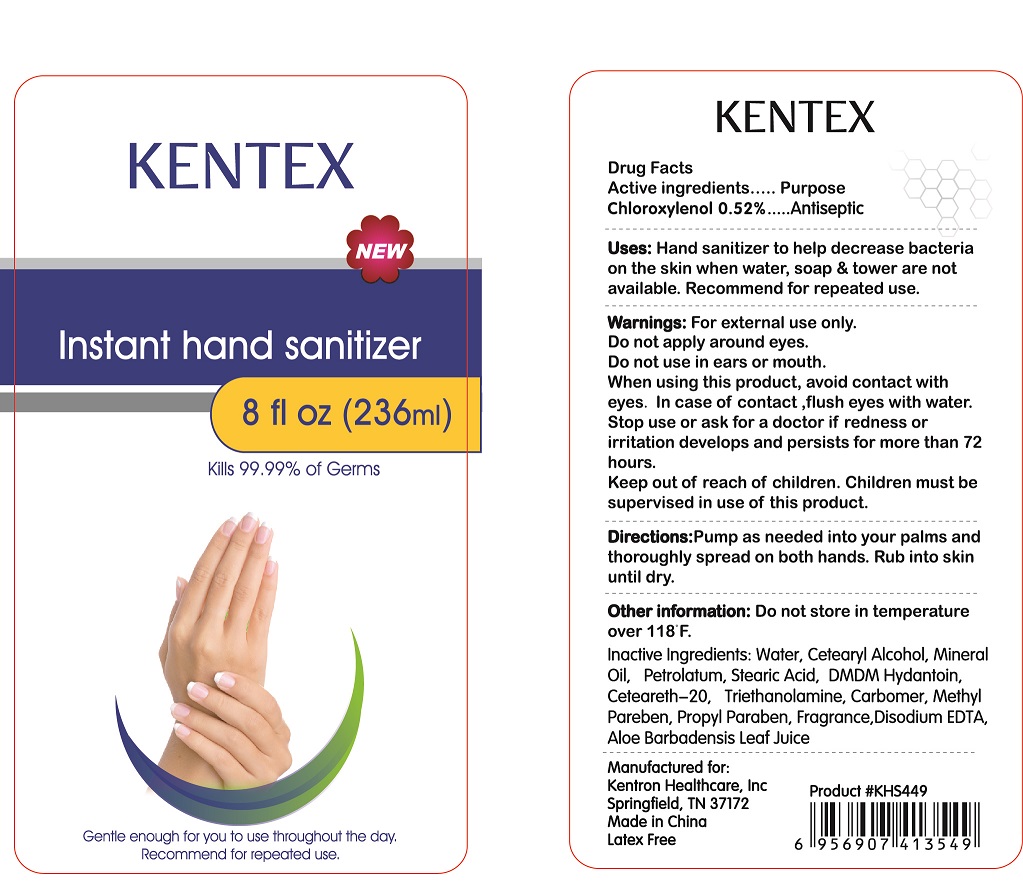 DRUG LABEL: Instant Hand Sanitizer
NDC: 69556-002 | Form: GEL
Manufacturer: Kentron Healthcare, Inc.
Category: otc | Type: HUMAN OTC DRUG LABEL
Date: 20170504

ACTIVE INGREDIENTS: CHLOROXYLENOL 5 mg/1 mL
INACTIVE INGREDIENTS: WATER; ALOE VERA LEAF; METHYLPARABEN; CARBOMER INTERPOLYMER TYPE A (55000 CPS); TROLAMINE; STEARIC ACID; DMDM HYDANTOIN; CETOSTEARYL ALCOHOL; MINERAL OIL; POLYOXYL 20 CETOSTEARYL ETHER; PETROLATUM; PROPYLPARABEN; EDETATE DISODIUM ANHYDROUS

Active ingredients
Chloroxylenol 0.52%

Purpose

Antiseptic

Warnings: For external use only.

Do not apply around eyes.

Do not use in ears or mouth.

When using this products, avoid contact with eyes. In case of contact, flush eyes with water.

Keep out of reach of children. Children must be supervised in use of this product.

Directions:

Pump as needed into your palms and thoroughly spread on both hands.

Rub into skin until dry.

INACTIVE INGREDIENT

Inactive Ingredients:Water, Cetearyl Alcohol, Mineral Oil, Petrolatum, Stearic Acid, DMDM Hydantoin, Ceteareth-20, Triethanolamine, Carbomer, Methyl Pareben, Propyl Paraben, Fragrance, Disodium EDTA, Aloe Barbadensis Leaf Juice

INDICATIONS AND USAGE

Uses: Hand sanitizer to help decrease bacteria on the skin when water, soap & towel are not available. Recommended for repeated use.

Other information: Do not store in temperature above 118 F.

Stop use or ask for a doctor if redness or irritation develops and persists for more than 72 hours.